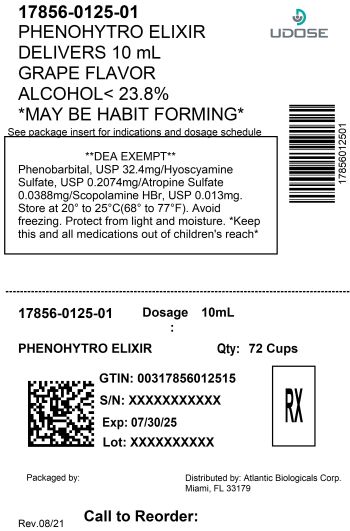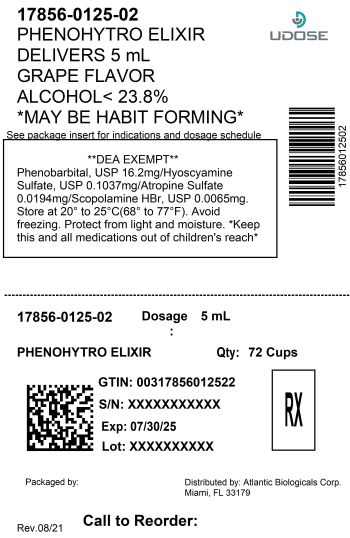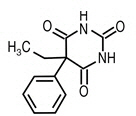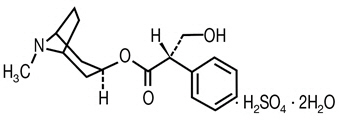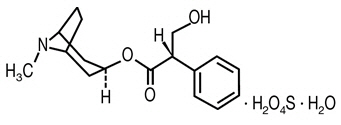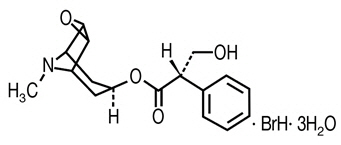 DRUG LABEL: Phenohytro
NDC: 17856-0125 | Form: ELIXIR
Manufacturer: ATLANTIC BIOLOGICALS CORP.
Category: prescription | Type: HUMAN PRESCRIPTION DRUG LABEL
Date: 20250922
DEA Schedule: CIV

ACTIVE INGREDIENTS: PHENOBARBITAL 16.2 mg/5 mL; HYOSCYAMINE SULFATE 0.1037 mg/5 mL; ATROPINE SULFATE 0.0194 mg/5 mL; SCOPOLAMINE HYDROBROMIDE 0.0065 mg/5 mL
INACTIVE INGREDIENTS: GLYCERIN 1981 mg/5 mL; ALCOHOL 407 mg/5 mL; WATER 2119 mg/5 mL; SUCROSE 289 mg/5 mL; SORBITOL 895 mg/5 mL; SACCHARIN SODIUM 28.9 mg/5 mL; FD&C RED NO. 3 0.075 mg/5 mL; FD&C BLUE NO. 1 0.005 mg/5 mL; GRAPE 2 mg/5 mL

PHENOHYTRO®ELIXIR

DEA EXEMPT - Rx Only

DESCRIPTION

PHENOHYTRO®ELIXIR Grape Flavored

each 5 mL (teaspoonful) oral-administered dose of elixir contains:

Phenobarbital, USP (WARNING:may be habit forming) | 16.2 mg
Hyoscyamine Sulfate, USP | 0.1037 mg
Atropine Sulfate, USP | 0.0194 mg
Scopolamine Hydrobromide, USP | 0.0065 mg
Alcohol not more than 23.8%

INACTIVE INGREDIENTS

Purified water, glycerin, sorbitol, ethyl alcohol, sucrose, sodium saccharin, artificial grape flavor, FD&C Red No. 3, FD&C Blue No. 1.

DESCRIPTION

PHENOHYTRO® ELIXIR Mint Flavored

each 5 mL (teaspoonful) oral-administered dose of elixir contains:

Phenobarbital, USP (WARNING:may be habit forming) | 16.2 mg
Hyoscyamine Sulfate, USP | 0.1037 mg
Atropine Sulfate, USP | 0.0194 mg
Scopolamine Hydrobromide, USP | 0.0065 mg
Alcohol not more than 23.8%

INACTIVE INGREDIENTS

Purified water, glycerin, sorbitol, ethyl alcohol, sucrose, sodium saccharin, artificial mint flavor, FD&C Yellow No. 5, FD&C Blue No. 1.

Phenobarbital is a barbiturate with the chemical name 2,4,6(1H,3H,5H) -Pyrimidinetrione, 5-ethyl-5-phenyl-. It has the following structural formula:

C12H12N2O3 Chemical Structure M.W. 232.2

Hyoscyamine sulfate is a belladonna alkaloid with the chemical name Benzeneacetic acid, α-(hydroxmethyl)-, 8-methyl-8-azabicyclo[3.2.1]oct-3-yl ester, [3(S)-endo]-, sulfate (2:1), dihydrate. It has the following structural formula:

(C17H23NO3)2 ∙ H2SO4 ∙ 2H2O Chemical Structure M.W. 712.85

Atropine sulfate is belladonna alkaloid with the chemical name: Benzeneacetic acid, α-(Hydroxymethyl)benzeneacetic acid 8-methyl-8-azabicyclo[3.2.1]oct-3-yl ester. It has the following structural formula:

(C34H46N2O6 ∙ H2O4S ∙ H2O Chemical Structure M.W. 694.83

Scopolamine hydrobromide is a belladonna alkaloid with the chemical name Benezeneacetic acid, α-(hydroxymethyl)-, 9-methyl-3-oxa-9-azatricyclo[3.31.0.2,4]non-[7-yl ester, hydrobromide, trihydrate, [7(S)-(1α,2β,4β,5α,7β)]-. It has the following structural formula:

C17H21NO4 ∙ BrH ∙ 3H2O Chemical Structure M.W. 438.31

CLINICAL PHARMACOLOGY

This drug combination provides phenobarbital combined with belladonna alkaloids in a specific, fixed ratio to provide anticholinergic/antispasmodic action and mild sedation.

Phenobarbital is a barbiturate, nonselective central nervous system depressant. It is primarily used as a sedative hypnotic and also as an anticonvulsant in subhypnotic doses.

Atropine Sulfate, Hyoscyamine Sulfate, and Scopolamine are belladonna alkaloids classified as anticholinergic, antimuscarinic drugs. They act to inhibit muscarinic actions of acetylcholine at postganglionic parasympathetic neuron effector sites. These drugs are also used as antispasmodics due to their anticholinergic action. They produce the effect in the body of reduced muscle spasms in the digestive or urinary tract, and reduced fluid secretions from certain glands or organs.

INDICATIONS AND USAGE

Based on the National Academy of Sciences-National Research Council's review of this drug and/or other information, FDA has classified the following indications as "possibly" effective: For use as adjunctive therapy in the treatment of irritable bowel syndrome (irritable colon, spastic colon, mucous colitis) and acute enterocolitis. May also be useful as adjunctive therapy in the treatment of duodenal ulcer.

IT HAS NOT BEEN SHOWN CONCLUSIVELY WHETHER ANTICHOLINERGIC / ANTISPASMODIC DRUGS AID IN THE HEALING OF A DUODENAL ULCER, DECREASE THE RATE OF RECURRENCES, OR PREVENT COMPLICATIONS.

CONTRAINDICATIONS

PHENOHYTRO®ELIXIR is contraindicated in patients with known hypersensitivity to any of the ingredients. Phenobarbital is contraindicated in patients with acute intermittent porphyria and in those patients in which phenobarbital produces restlessness and/or excitement.

PHENOHYTRO®ELIXIR is also contraindicated in patients with glaucoma, obstructive uropathy; paralytic ileus; myasthenia gravis; intestinal atony; unstable cardiovascular status in acute hemorrhage; severe ulcerative colitis especially if complicated by toxic megacolon; hiatal hernia associated with reflux esophagitis; obstructive disease of the gastrointestinal tract; or severe ulcerative colitis.

WARNINGS

Heat prostration can occur with belladonna alkaloids in high temperatures.

Diarrhea may be an early symptom of incomplete intestinal obstruction, particularly in patients with ileostomy or colostomy. In this instance, treatment with this drug could be harmful.

PHENOHYTRO®ELIXIR may produce drowsiness and blurred vision. The patient should be warned about engaging in hazardous work or activities requiring mental alertness, such as operating a motor vehicle or other machinery.

Phenobarbital may decrease the effect of anticoagulants, and larger doses of the anticoagulant may be necessary for optimal effect. When phenobarbital is discontinued, the dose of the anticoagulant may have to be decreased.

Phenobarbital may be habit formingand should not be administered to patients who are susceptible to addiction or to those with a history of physical and/or psychological drug dependence.

Barbiturates should be used with caution in patients with hepatic dysfunction.

PRECAUTIONS

GENERAL

Use with caution in patients with: autonomic neuropathy, hepatic or renal disease, hyperthyroidism, coronary heart disease, congestive heart failure, cardiac arrhythmias, tachycardia, and hypertension.

Belladonna alkaloids may produce a delay in gastric emptying (antral stasis), which would complicate the management of gastric ulcer.

Do not rely on the use of the drug in the presence of complication of biliary tract disease. Theoretically, a curare-like action may occur with overdosage.

CARCINOGENESIS, MUTAGENESIS, IMPAIRMENT OF FERTILITY

Long-term studies in animals have not been performed to evaluate carcinogenic potential.

PREGNANCY

PREGNANCY CATEGORY C

Animal reproduction studies have not been conducted with PHENOHYTRO®ELIXIR. It is not known whether PHENOHYTRO®ELIXIR can cause fetal harm when administered to a pregnant woman or can affect reproduction capacity. PHENOHYTRO®ELIXIR should be given to a pregnant woman only if clearly needed.

NURSING MOTHERS

It is not known whether this drug is excreted in human milk. Because many drugs are excreted in human milk, exercise caution when administering PHENOHYTRO®ELIXIR to a nursing woman.

INFORMATION FOR PATIENTS

Practitioners should give the following information and instructions to patients:

- Do not increase the dose of this drug without consulting a physician.
- Do not share this medication with others.
- The use of this product carries with it an associated risk of psychological and/or physical dependence.
- The use of this product may impair mental and/or physical abilities required for the performance of potentially hazardous tasks such as driving or operating machinery.
- Use of this product with alcohol may result in additional central nervous system depressant effects.
- Tell your doctor or pharmacist if you also take antihistamines, anti-seizure drugs, medicine for sleep or anxiety, muscle relaxants, narcotic pain relievers, or psychiatric medicines.
- This drug may increase the risk for heatstroke because it decreases sweating. Avoid becoming overheated in hot weather, saunas, and during exercise or other strenuous activity.

ADVERSE REACTIONS

Call your doctor for medical advice about side effects.

Adverse reactions associated with anticholinergics and/or anticonvulsants are: dry mouth; tachycardia; urinary hesitancy and retention; palpitation; blurred vision; prolonged pupil dilation; cycloplegia; increased ocular tension; loss of taste sense; headache; nervousness; drowsiness; weakness; dizziness; insomnia; nausea; vomiting; severe allergic reaction or drug idiosyncrasies, including anaphylaxis, hives and/or other dermal manifestations; decreased sweating; impotence; suppression of lactation; constipation; bloated feeling and musculoskeletal pain. Elderly patients may react with symptoms of excitement, agitation and drowsiness to even small doses of the drug. Phenobarbital may produce excitement in some patients, rather than a sedative effect. In patients habituated to barbiturates, abrupt withdrawal may produce delirium or convulsions.

To report SUSPECTED ADVERSE REACTIONS, contact FDA at 1-800-FDA-1088 or www.fda.gov/medwatch.

OVERDOSAGE

The signs and symptoms of overdose are headache, nausea, vomiting, blurred vision, dilated pupils, hot and dry skin, dizziness, dryness of the mouth, difficulty in swallowing, and CNS stimulation. Call your doctor or local Poison Control Center if overdosage is suspected.

The dosage of PHENOHYTRO®ELIXIR should be adjusted to the needs of the individual patient to assure symptomatic control with a minimum of adverse effects.

DOSAGE AND ADMINISTRATION

Adults

One or two teaspoonfuls of PHENOHYTRO®ELIXIR three or four times a day according to conditions and severity of symptoms.

Pediatric patients

may be dosed every 4 to 6 hours.

Starting Dosage
Body Weight | q4h | q6h
10 lb. (4.5 kg) | 0.5 mL | 0.75 mL
20 lb. (9.1 kg) | 1.0 mL | 1.5 mL
30 lb. (13.6 kg) | 1.5 mL | 2.0 mL
50 lb. (22.7 kg) | 1/2 tsp | 3/4 tsp
75 lb. (34 kg) | 3/4 tsp | 1 tsp
100 lb. (45.4kg) | 1 tsp | 1 1/2 tsp

HOW SUPPLIED

PHENOHYTRO®ELIXIR Grape Flavored is a purple colored, grape flavored liquid.

NDC 17856-0125-01 Grape Flavored in 10mL 72 CUP

NDC 17856-0125-02 Grape Flavored in 5mL 72 CUP

STORAGE CONDITIONS

AVOID FREEZING

Store PHENOHYTRO®ELIXIR at 20° - 25°C (68° - 77°F) [see USP Controlled Room Temperature].

Protect from light and moisture.

Dispense in a tight, light-resistant container as defined in the USP using a child-resistant closure. Use safety closures when dispensing this product unless otherwise directed by a physician or requested by purchaser.

WARNINGS: KEEP THIS AND ALL DRUGS OUT OF THE REACH OF CHILDREN.

IN THE CASE OF OVERDOSE, SEEK PROFESSIONAL ASSISTANCE OR CONTACT A POISON CONTROL CENTER IMMEDIATELY.

Contains color additives, including FD&C Yellow No. 5 (tartrazine).

DISTRIBUTED BY:

ATLANTIC BIOLOGICALS CORP.

20101 N.E 16TH PLACE

MIAMI, FL 33179

PRINCIPAL DISPLAY PANEL

NDC 17856-0125-02

Phenohytro®

Elixir 5mL CUP

Grape Flavored

Each 5 mL (1 teaspoonful) contains:

Phenobarbital, USP
16.2 mg

Hyoscyamine Sulfate, USP
0.1037 mg

Atropine Sulfate, USP
0.0194 mg

Scopolamine Hydrobromide, USP
0.0065 mg

Alcohol not more than 23.8

DEA EXEMPT Rx Only

PRINCIPAL DISPLAY PANEL -

NDC 17856-0125-01

Phenohytro®

Elixir 10mL CUP

Grape Flavored

Each 5 mL (1 teaspoonful) contains:

Phenobarbital, USP
16.2 mg

Hyoscyamine Sulfate, USP
0.1037 mg

Atropine Sulfate, USP
0.0194 mg

Scopolamine Hydrobromide, USP
0.0065 mg

Alcohol not more than 23.8%

DO NOT USE IF TAMPER-EVIDENT SEAL
UNDER CAP IS BROKEN OR MISSING

DEA EXEMPT Rx Only